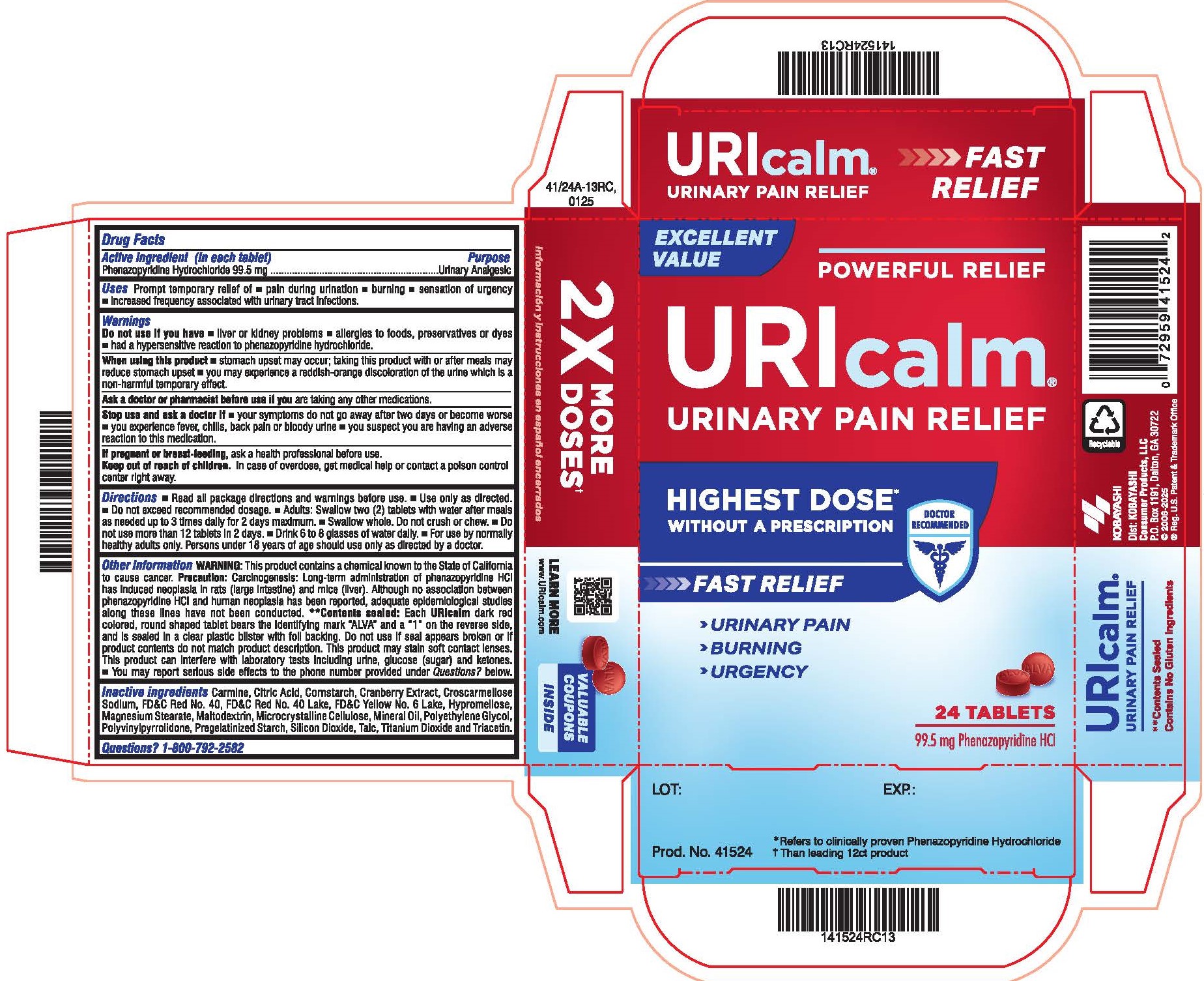 DRUG LABEL: Uricalm
NDC: 52389-241 | Form: TABLET, FILM COATED
Manufacturer: Kobayashi Healthcare International, Inc.
Category: otc | Type: HUMAN OTC DRUG LABEL
Date: 20250328

ACTIVE INGREDIENTS: PHENAZOPYRIDINE HYDROCHLORIDE 99.5 mg/1 1
INACTIVE INGREDIENTS: CITRIC ACID; FD&C RED NO. 40 ALUMINUM LAKE; FD&C YELLOW NO. 6 ALUMINUM LAKE; COCHINEAL; HYPROMELLOSES; LIGHT MINERAL OIL; TITANIUM DIOXIDE; FD&C RED NO. 40; TRIACETIN; CROSCARMELLOSE SODIUM; MAGNESIUM STEARATE; CELLULOSE, MICROCRYSTALLINE; POVIDONE; SILICON DIOXIDE; POLYETHYLENE GLYCOL 400; TALC; STARCH, CORN; CRANBERRY; MALTODEXTRIN

Uricalm

Active ingredient (in each tablet)

Phenazopyridine hydrochloride, 99.5 mg

Purpose

Urinary Analgesic

Uses

Prompt temporary relief of:

- pain during urination
- burning
- sensation of urgency
- increased frequency

associated with urinary tract infections.

Do not use if you have

- liver or kidney problems
- allergies to foods, preservatives or dyes
- had a hypersensitive reaction to phenazopyridine hydrochloride.

When using this product

- stomach upset may occur; taking this product with or after meals may reduce stomach upset
- you may experience a reddish-orange discoloration of the urine which is a non-harmful temporary effect.

Ask a doctor or pharmacist before use if you are taking any other medications.

Stop use and ask a doctor if

- your symptoms do not go away after two days or become worse
- you experience fever, chills, back pain or bloody urine
- you suspect you are having an adverse reaction to this medication.

PREGNANCY OR BREAST FEEDING

If pregnant or breastfeeding, ask a health professional before use.

Keep out of reach of children. In case of overdose, get medical help or contact a poison control center right away.

Directions

- Read all package directions and warnings before use.
- Use only as directed.
- Do not exceed recommended dosage.
- Adults: Swallow two (2) tablets with water after meals as needed up to 3 times daily for 2 days maximum.
- Swallow whole. Do not crush or chew.
- Do not use more than 12 tablets in 2 days.
- Drink 6 to 8 eight glasses of water daily.
- For use by normally healthy adults only. Persons under 18 years of age should use only as directed by a doctor.

Other information

WARNING: this product contains a chemical known to the State of California to cause cancer. Precaution: Carcinogenesis: Long-term administration of phenazopyridine HCl has induced neoplasia in rats (large intestine) and mice (liver) . Although no association between phenazopyridine HCl and human neoplasia has been reported, adequate epidemiological studies along these lines have not been conducted. **Contents sealed: Each URICALM dark red colored, round shaped tablet bears the identifying mark "ALVA" and a "1" on the reverse side, and is sealed in a clear plastic blister with with foil backing. Do not use if seal appears broken or if product contents do not match product description. This product may stain soft contact lenses. This product can interfere with laboratory tests including urine, glucose (sugar) and ketones. You may report serious side effects to the phone number provided under Questions? below.

Inactive ingredients

Carmine, Citric Acid, Cornstarch, Cranberry Extract, Croscarmellose Sodium, FD&C Red No. 40, FD&C Red No. 40 Lake, FD&C Yellow No. 6 Lake, Hypromellose, Magnesium Stearate, Maltodextrin, Microcrystalline Cellulose, Mineral Oil, Polyethylene Glycol, Polyvinylpyrrolidone, Pregelatinized Starch, Silicon Dioxide, Talc, Titanium Dioxide and Triacetin.

Questions? 1-800-792-2582.

Product Insert

Uricalm

199 mg Strong per dose

The Highest Dose of Clinically Proven Phenazopyridine Hydrochloride Available Over the Counter, Plus Cranberry

URICALM provides the maximum non-prescription strength of clinically proven Phenazopyridine Hydrochloride to relieve pain, burning, increased frequency, and sensation of urgency associated with urinary tract infections. Phenazopyridine Hydrochloride is the #1 doctor recommended ingredient for fast relief of UTI pain. Plus, URICALM contains cranberry, which is used extensively by those concerned about urinary tract health.

Active ingredient (in each tablet):Phenazopyridine Hydrochloride 99.5 mg

Purpose: Urinary analgesic

Uses: Prompt temporary relief of

- pain during urination
- burning
- sensation of urgency
- increased frequency associated with urinary tract infections.

Warnings

Do not use if you have

- liver or kidney problems
- allergies to foods, preservatives or dyes
- had a hypersensitive reaction to phenazopyridine hydrochloride

When using this product

- stomach upset may occur; taking this product with or after meals may reduce stomach upset
- you may experience a reddish-orange discoloration of the urine which is a non-harmful temporary effect.

Ask a doctor or pharmacist before use if you are taking any other medications.

Stop use and ask a doctor if

- your symptoms do not go away after two days or become worse
- you experience fever, chills, back pain or bloody urine.
- you suspect you are having an adverse reaction to this medication

If pregnant or breast-feeding, ask a health professional before use.

Keep out of reach of children. In case of overdose, get medical help or contact a poison control center right away.

Directions:

- Read all package directions and warnings before use.
- Use only as directed.
- Do not exceed recommended dosage.
- Adults: Swallow two (2) tablets with water after meals as needed up to 3 times daily for 2 days maximum.
- Swallow whole. Do not crush or chew.
- Do not use more than 12 tablets in 2 days
- Drink 6 to 8 glasses of water daily.
- For use by normally healthy persons only. Persons under 18 years of age should use only as directed by a doctor.

Other information: WARNING: This product contains a chemical known to the State of California to cause cancer. Precaution: Carcinogenesis: Long-term administration of phenazopyridine HCl has induced neoplasia in rats (large intestine) and mice (liver). Although no association between phenazopyridine HCl and human neoplasia has been reported, adequate epidemiological studies along these lines have not been conducted.

**Contents sealed: Each URICALM dark red colored, round shaped tablet bears the identifying mark "ALVA" and a "1" on the reverse side, and is sealed in a clear plastic blister with foil backing. Do not use if seal appears broken or if product contents do not match product description. This product may stain soft contact lenses. This product can interfere with laboratory tests including urine, glucose (sugar) and ketones. You may report serious side effects to the phone number provided under Questions? below.

Inactive ingredients:Carmine, citric acid, corn starch, cranberry fruit extract, croscarmellose sodium, FD&C Red No. 40, FD&C Red No. 40 Lake, FD&C Yellow No. 6 Lake, hypromellose, magnesium stearate, maltodextrin, microcrystalline cellulose, mineral oil, polyethylene glycol, polyvinylpyrrolidone, pregelatinized starch, silicon dioxide, talc, titanium dioxide and triacetin.

Questions? 1-800-792-2582

www.URICALM.com

Uricalm

199 mg de concentración por dosis

Contiene la dosis más alta de phenazopyridine hydrochloride clínicamente comprobado disponible en venta sin receta, además de arándano

URICALM ofrece la dosis más alta de chlorhidrato de fenazopyridina clínicamente comprobado de venta sin receta para aliviar el dolor, el ardor, el aumento en la frequencia y la sensación de necesidad urgente de orinar asociados con las infecciones del tracto urinario. El chlorhidrato de fenazopiridina es el ingrediente N.o 1 recomendado por el médico para el alivio rápido del dolor causado por las infecciones del tracto urinario (UTI, por sus singlas en ingles). Además, URICALM contiene arándano, que es usado ampliamente por quienes se preocupan por la salud del tracto urinario.

Ingrediente activo (in cada tableta): Phenazopyridine hydrochloride 99.5 mg

Propósito: Analgésico urinario

Usos: Alivio rápido y temporal del

- dolor durante la micción
- del ardor
- de la sensación de necesidad urgente de orinar
- del aumento en la frecuencia asociada con las infecciones del tracto urinario.

Advertencias:

No lo use si tiene

- problemos hepático o renales
- alergias a los alimentos, conservantes o colorantes
- ha tenido una reacción hipersensible al phenazopyridine hydrochloride

Cuando se use este producto

- puede presentarse malestar estomical; la ingestión de este producto con alimentos o después de comer puede reducir el malestar estomacal
- puede experimentar un color de rojizo a anaranjado en la orina, lo cual es un efecto temporal inofensivo.

Consulte con un médico o farmacéutico antes de usarlo si está tomando cualquier otro medicamento.

Interrumpa el uso y consulte con su médico si

- los síntomas no desaparecen o empeoran después de dos dias
- tiene fiebre, escalofríos, dolor de espalda o nota la presencia de sangre en la orina.
- sospecha que está experimentado una reacción adversa a este medicamento.

Si está embarazada o lactando, consulte con un profesional de la salud antes de usario.

Manténgalo fuera del alcance de los niños. En caso de sobredosis, obtenga ayuda médica o comuníquese de inmediato con un centro de toxicologia.

Indicaciones:

- Lea todos las indicaciones y advertencias en el envase antes de usarlos.
- Úselo únicamente como se indica.
- No exceda la dosis recomendada.
- Adultos: Ingiera dos (2) tabletas con agua después de las comidas según sea necesario hasta 3 veces al día por un máximo de 2 dias.
- Trague la tablets entera. No triture ni mastique la tableta.
- No use más de 12 tabletas en 2 días.
- Tome de 6 a 8 vasos de agua todos los dias.
- Para usarlo en adultos normalmente sanos únicamente. Las personas menores de 18 años deben usarlo solo según las indicaciones de un médico.

Información adicional: ADVERTENCIA: Este producto contiene una sustancia quimica que en el Estado de California se sabe que causa cáncer. Precaución: Carcinogénesis: La administración a largo plazo del phenazopyridine hydrochloride ha inducido neoplasia en ratas (intestino grueso) y en ratones (hígado). Aunque no ha sido informada una asociación entre el phenazopyridine hydrochloride y la neoplasia en seres humanos, no se han realizado estudios epidemiológicos adecuados sobre esto.

**El contenido está sellado Cada tableta URICALM de color rojo oscuro y redonda lleva la marca identificadora "ALVA" y un "1" en el dorso, y está sellada en un blíster de plástico transperente con un recubrimiento posterior de papel aluminio. No lo use si el sello parece estar roto o si el producto no coincide con la descripción del producto. Este producto puede causar manchas en los lentes de contacto blandos. Este producto puede interferir con las pruebas de laboratorio incluidas orina, glucosa (azúcar) y cetonas. Puede informar efectos secundarios graves al número de teléfono que aparece en la sección ¿Tiene preguntas? a continuación.

Ingredientes inactivos: carmin, ácido cítrico, almidón de maíz, extracto de arándano, croscarmelosa sódica, FD&C Rojo No. 40, FD&C Rojo No. 40 Lake, FD&C Amarillo No. 6 lake, hipromelosa, estearato de magnesio, maltodextrina, celulosa microcristalina, aceite mineral, polietilenglicol, polivinilpirrolidona, almidón pregelatinizado, dióxido de silicio, talco, dióxido de titanio y tracetino.

¿Tiene preguntas? 1-800-792-2582

www.URICALM.com